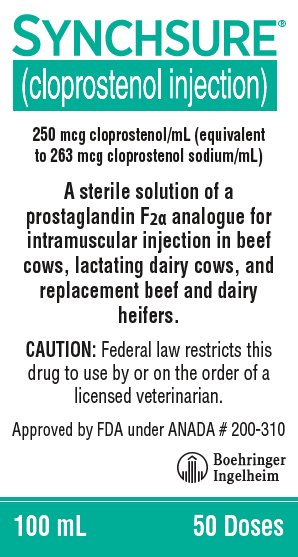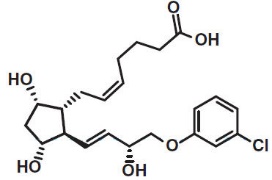 DRUG LABEL: SYNCHSURE
NDC: 0010-3549 | Form: INJECTION, SOLUTION
Manufacturer: Boehringer Ingelheim Animal Health USA Inc.
Category: animal | Type: PRESCRIPTION ANIMAL DRUG LABEL
Date: 20250103

ACTIVE INGREDIENTS: cloprostenol sodium 250 ug/1 mL
INACTIVE INGREDIENTS: CHLOROCRESOL 1 mg/1 mL; ANHYDROUS CITRIC ACID 0.66 mg/1 mL; sodium citrate, unspecified form 5.03 mg/1 mL; sodium chloride 6.76 mg/1 mL

SYNCHSURE®
(cloprostenol injection)

Approved by FDA under ANADA # 200-310

250 mcg cloprostenol/mL (equivalent to 263 mcg cloprostenol sodium/mL)

A sterile solution of a prostaglandin F2α analogue for intramuscular injection in beef cows, lactating dairy cows, and replacement beef and dairy heifers

CAUTION:

Federal law restricts this drug to use by or on the order of a licensed veterinarian.

DESCRIPTION:

SYNCHSURE (cloprostenol injection) is a synthetic prostaglandin analogue structurally related to prostaglandin F2α (PGF2α). Each mL of the sterile colorless aqueous solution contains 250 mcg cloprostenol (equivalent to 263 mcg cloprostenol sodium), 5.03 mg sodium citrate, 0.66 mg anhydrous citric acid, 6.76 mg sodium chloride, 1.0 mg chlorocresol, and water for injection q.s.

INDICATIONS FOR USE:

1. For unobserved or non-detected estrus in beef cows, lactating dairy cows, and replacement beef and dairy heifers

2. For treatment of pyometra or chronic endometritis in beef cows, lactating dairy cows, and replacement beef and dairy heifers

3. For treatment of mummified fetus in beef cows, lactating dairy cows, and replacement beef and dairy heifers

4. For treatment of luteal cysts in beef cows, lactating dairy cows, and replacement beef and dairy heifers

5. For abortion of beef cows, lactating dairy cows, and replacement beef and dairy heifers

6. For estrus synchronization in beef cows, lactating dairy cows, and replacement beef and dairy heifers

7. For use with gonadorelin to synchronize estrous cycles to allow for fixed time artificial insemination (FTAI) in lactating dairy cows

SYNCHSURE causes functional and morphological regression of the corpus luteum (luteolysis) in cattle. In normal, non-pregnant cycling animals, this effect on the life span of the corpus luteum usually results in estrus 2 to 5 days after treatment. In animals with prolonged luteal function (pyometra, mummified fetus, and luteal cysts), the induced luteolysis usually results in resolution of the condition and return to cyclicity. Pregnant animals may abort depending on the stage of gestation.

DOSAGE AND ADMINISTRATION:

Two mL of SYNCHSURE (500 mcg cloprostenol) should be administered by INTRAMUSCULAR INJECTION using the specific dosage regimen for the indication.

Discard remaining product 180 days after first use.

1. For unobserved or non-detected estrus in beef cows, lactating dairy cows, and replacement beef and dairy heifers

Cows and heifers which are not detected in estrus, although ovarian cyclicity continues, can be treated with SYNCHSURE if a mature corpus luteum is present. Estrus is expected to occur 2 to 5 days following injection, at which time animals may be inseminated. Treated cattle should be inseminated at the usual time following detection of estrus. If estrous detection is not desirable or possible, treated animals may be inseminated twice at about 72 and 96 hours post-injection.

2. For treatment of pyometra or chronic endometritis in beef cows, lactating dairy cows, and replacement beef and dairy heifers

Damage to the reproductive tract at calving or postpartum retention of the placenta often leads to infection and inflammation of the uterus (endometritis). Under certain circumstances, this may progress into chronic endometritis with the uterus becoming distended with purulent matter. This condition, commonly referred to as pyometra, is characterized by a lack of cyclical estrous behavior and the presence of a persistent corpus luteum. Induction of luteolysis with SYNCHSURE usually results in evacuation of the uterus and a return to normal cyclical activity within 14 days after treatment. After 14 days post-treatment, recovery rate of treated animals will not be different than that of untreated cattle.

3. For treatment of mummified fetus in beef cows, lactating dairy cows, and replacement beef and dairy heifers

Death of the conceptus during gestation may be followed by its degeneration and dehydration. Induction of luteolysis with SYNCHSURE usually results in expulsion of the mummified fetus from the uterus. (Manual assistance may be necessary to remove the fetus from the vagina). Normal cyclical activity usually follows.

4. For treatment of luteal cysts in beef cows, lactating dairy cows, and replacement beef and dairy heifers

A cow or heifer may be noncyclic due to the presence of a luteal cyst (a single, anovulatory follicle with a thickened wall which is accompanied by no external signs and by no changes in palpable consistency of the uterus). Treatment with SYNCHSURE can restore normal ovarian activity by causing regression of the luteal cyst.

5. For abortion of beef cows, lactating dairy cows, and replacement beef and dairy heifers

Unwanted pregnancies can be safely and efficiently terminated from 1 week after mating until about 5 months of gestation. The induced abortion is normally uncomplicated and the fetus and placenta are usually expelled about 4 to 5 days after the injection with the reproductive tract returning to normal soon after the abortion. The ability of SYNCHSURE to induce abortion decreases beyond the fifth month of gestation while the risk of dystocia and its consequences increases. SYNCHSURE has not been sufficiently tested under feedlot conditions; therefore recommendations cannot be made for its use in heifers placed in feedlots.

6. For estrus synchronization in beef cows, lactating dairy cows, and replacement beef and dairy heifers

The luteolytic action of SYNCHSURE can be utilized to schedule estrus and ovulation for an individual cycling animal or a group of animals. This allows control of the time at which cycling cows or heifers can be bred. SYNCHSURE can be used in a breeding program with the following methods:

- Single SYNCHSURE injection: Only animals with a mature corpus luteum should be treated to obtain maximum response to the single injection. However, not all cycling cattle should be treated since a mature corpus luteum is present for only 11 to 12 days of the 21-day cycle. Prior to treatment, cattle should be examined rectally and found to be anatomically normal, be nonpregnant, and have a mature corpus luteum. If these criteria are met, estrus is expected to occur 2 to 5 days following injection, at which time animals may be inseminated. Treated cattle should be inseminated at the usual time following detection of estrus. If estrous detection is not desirable or possible, treated animals may be inseminated either once at about 72 hours or twice at about 72 and 96 hours post-injection.
  With a single injection program, it may be desirable to assess the cyclicity status of the herd before SYNCHSURE treatment. This can be accomplished by heat detecting and breeding at the usual time following detection of estrus for a 6-day period, all prior to injection. If by the sixth day the cyclicity status appears normal (approximately 25 - 30% detected in estrus), all cattle not already inseminated should be palpated for normality, nonpregnancy, and cyclicity, then injected with SYNCHSURE. Breeding should then be continued at the usual time following signs of estrus on the seventh and eighth days. On the ninth and tenth days, breeding may continue at the usual time following detection of estrus, or all cattle not already inseminated may be bred either once on the ninth day (at about 72 hours post-injection) or on both the ninth and tenth days (at about 72 and 96 hours post-injection).
- Double SYNCHSURE injections: Prior to treatment, cattle should be examined rectally and found to be anatomically normal, nonpregnant, and cycling (the presence of a mature corpus luteum is not necessary when the first injection of a double injection regimen is given). A second injection should be given 11 days after the first injection. In normal, cycling cattle, estrus is expected 2 to 5 days following the second injection. Treated cattle should be inseminated at the usual time following detection of estrus. If estrous detection is not desirable or possible, treated animals may be inseminated either once at about 72 hours or twice at about 72 and 96 hours following the second SYNCHSURE injection. Many animals will come into estrus following the first injection; these animals can be inseminated at the usual time following detected estrus. Animals not inseminated should receive a second injection 11 days after the first injection. Animals receiving both injections may be inseminated at the usual time following detection of estrus or may be inseminated either once at about 72 hours or twice at about 72 and 96 hours post second injection.

Any breeding program recommended should be completed by either:

- observing animals (especially during the third week after injection) and inseminating or hand mating any animals returning to estrus,
  or
- turning in clean-up bull(s) 5 to 7 days after the last injection of SYNCHSURE to cover any animals returning to estrus.

Management considerations for use of SYNCHSURE for estrus synchronization:
A variety of programs can be designed to best meet the needs of individual management systems. A breeding program should be selected which is appropriate for the existing circumstances and management practices. Before a breeding program is planned, the producer’s objectives must be examined and the producer must be made aware of the projected results and limitations. The producer and the consulting veterinarian should review the operation’s breeding history, herd health, and nutritional status and agree that a breeding program is practical in the producer’s specific situation. For any successful breeding program:

- cows and heifers must be normal, non-pregnant, and cycling (rectal palpation should be performed);
- cows and heifers must be in sound breeding condition and on an adequate or increasing plane of nutrition;
- proper program planning and record keeping are essential;
- if artificial insemination is used, it must be performed by competent inseminators using high-quality semen.

It is important to understand that SYNCHSURE is effective only in animals with a mature corpus luteum (ovulation must have occurred at least 5 days prior to treatment). This must be considered when breeding is intended following a single SYNCHSURE injection.

There is no difference in the fertility achieved following the single or double dosage regimen when breeding occurs at induced estrus or at 72 and 96 hours post-treatment. Conception rates may be lower than expected in those fixed time breeding programs employing SYNCHSURE alone which omit the second insemination (ie, the insemination at or near 96 hours). This is especially true if a fixed time insemination is used following a single SYNCHSURE injection.

7. For use with gonadorelin to synchronize estrous cycles to allow for fixed time artificial insemination (FTAI) in lactating dairy cows

Use in reproductive synchrony programs similar to the following:

- Administer the first gonadorelin injection by intramuscular injection on Day 0.
- Administer 2 mL of SYNCHSURE by intramuscular injection 6 to 8 days after the first gonadorelin injection.
- Administer the second gonadorelin injection 30 to 72 hours after the SYNCHSURE injection.
- Perform FTAI 8 to 24 hours after the second gonadorelin injection, or inseminate cows on detected estrus using standard herd practices.

CONTRAINDICATIONS:

Do not use this drug product in pregnant cattle, unless abortion is desired.

WARNINGS AND PRECAUTIONS:

WITHDRAWAL PERIODS AND RESIDUE WARNINGS:

No milk discard or pre-slaughter drug withdrawal period is required when used according to labeling. Use of this product in excess of the approved dose may result in drug residues.

USER SAFETY WARNINGS:

Not for use in humans. Keep this and all drugs out of the reach of children.

Women of childbearing age, asthmatics, and persons with bronchial and other respiratory problems should exercise extreme caution when handling this product.

SYNCHSURE is readily absorbed through the skin and can cause abortion and/or bronchospasms. Direct contact with the skin should therefore be avoided. Accidental spillage on the skin should be washed off immediately with soap and water.

The Safety Data Sheet (SDS) contains more detailed occupational safety information. To obtain an SDS or for technical assistance, contact Boehringer Ingelheim Animal Health USA Inc. at 1-888-637-4251.

ANIMAL SAFETY WARNINGS:

As with all parenteral products, careful aseptic techniques should be employed to decrease the possibility of post-injection bacterial infection. Severe localized clostridial infections associated with injection of cloprostenol injection have been reported. In rare instances, such infections have resulted in death. Aggressive antibiotic therapy should be employed at the first sign of infection at the injection site, whether localized or diffuse.

At 50 and 100 times the recommended dose, mild side effects may be detected in some cattle. These include increased uneasiness, slight frothing, and milk let-down.

CONTACT INFORMATION:

To report suspected adverse drug experiences, contact Boehringer Ingelheim Animal Health USA Inc. at 1-888-637-4251. For additional information about adverse drug experience reporting for animal drugs, contact FDA at 1-888-FDA-VETS or http://www.fda.gov/reportanimalae

HOW SUPPLIED:

100 mL multidose vials

STORAGE, HANDLING, AND DISPOSAL:

1. Protect from light.

2. Store in carton.

3. Store at controlled room temperature 20°-25°C (68°-77°F).

See FDA’s website http://www.fda.gov/safesharpsdisposal for information on safe disposal of needles and other sharps.

Distributed by:
Boehringer Ingelheim Animal Health USA Inc.
Duluth, GA 30096

Approved by FDA under ANADA # 200-310

SYNCHSURE® is a registered trademark of Boehringer Ingelheim Animal Health USA Inc.
© 2024 Boehringer Ingelheim Animal Health USA Inc. All rights reserved.

100 mL: 50434-01

1050-8918-03 Rev. 05-2024